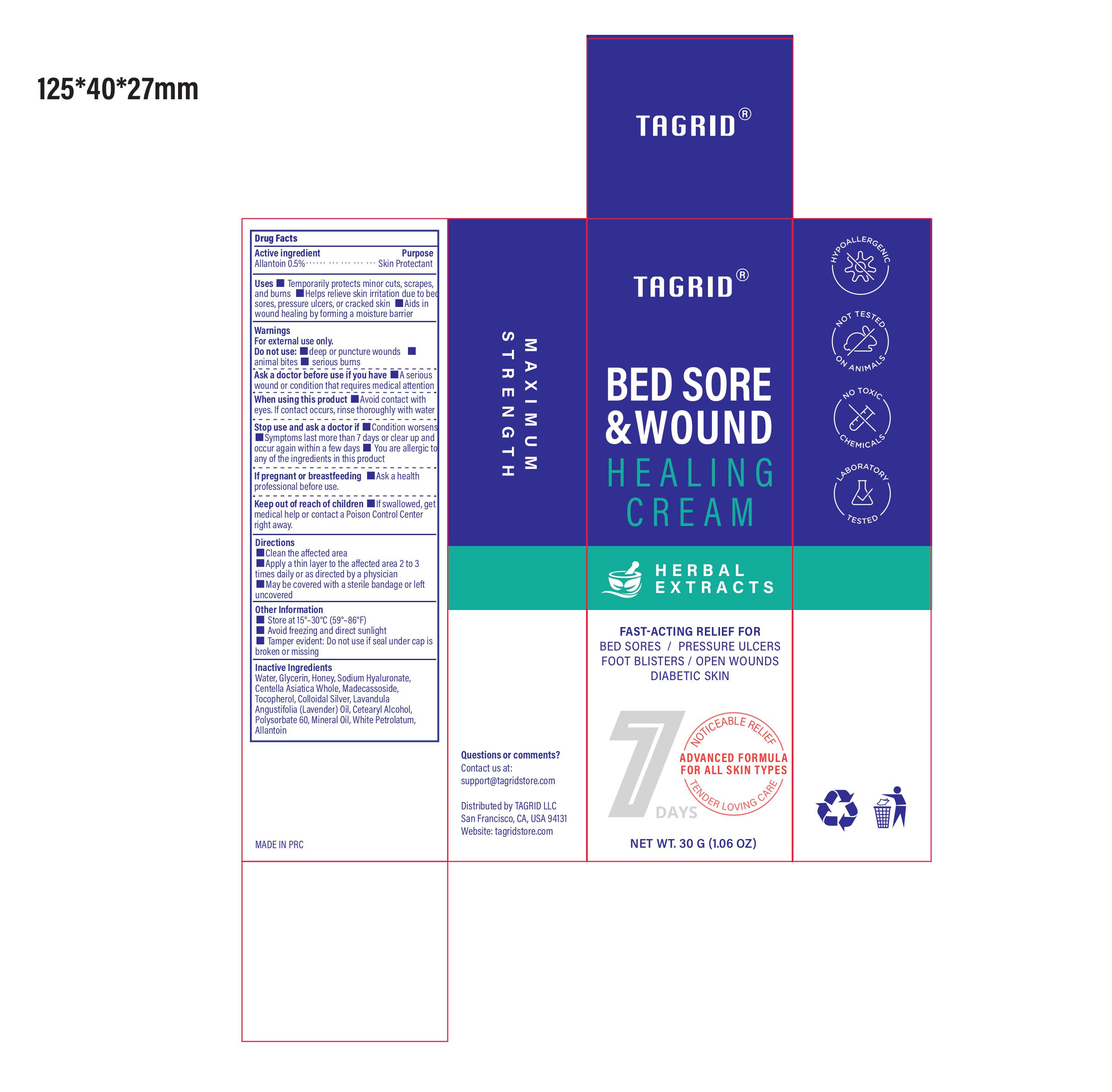 DRUG LABEL: Bed Sore and Wound Healing Cream
NDC: 85384-0011 | Form: CREAM
Manufacturer: TAGRID LLC
Category: otc | Type: HUMAN OTC DRUG LABEL
Date: 20250614

ACTIVE INGREDIENTS: ALLANTOIN 5 mg/1 g
INACTIVE INGREDIENTS: COLLOIDAL SILVER; WATER; TOCOPHEROL; MADECASSOSIDE; CENTELLA ASIATICA WHOLE; SODIUM HYALURONATE; HONEY; POLYSORBATE 60; CETEARYL ALCOHOL; MINERAL OIL; WHITE PETROLATUM; GLYCERIN; LAVANDULA ANGUSTIFOLIA (LAVENDER) OIL

Active ingredient:

1. Allantoin 0.5%

PURPOSE

1. Skin Protectant

Uses:

1. Temporarily protects minor cuts, scrapes, and burns
2. Helps relieve skin irritation associated with bed sores, pressure ulcers, or cracked skin
3. Aids in the healing of wounds by forming a protective moisture barrier

WARNINGS

For external use only

Do not use:

- On deep or puncture wounds
- On animal bites
- On serious burns

Ask a doctor before use if you have:

A serious wound or condition that requires medical attention

When using this product

Avoid contact with eyes. If contact occurs, rinse thoroughly with water.

Stop use and ask a doctor if

- Condition worsens
- Symptoms last more than 7 days or clear up and occur again within a few days
- You are allergic to any of the ingredients in this product

If pregnant or breast-feeding

Ask a health professional before use

Keep out of reach of children.

If swallowed, get medical help or contact a Poison Control Center right away.

Directions:

- Clean the affected area
- Apply a thin layer to the affected area 2 to 3 times daily or as directed by a physician
- May be covered with a sterile bandage or left uncovered

Other information:

- Store at 15°–30°C (59°–86°F)
- Avoid freezing and direct sunlight
- Tamper-evident: Do not use if seal under cap is broken or missing

Inactive ingredients:

- Colloidal Silver
- Water
- Tocopherol
- Madecassoside
- Centella Asiatica Whole
- Sodium Hyaluronate
- Honey
- Polysorbate 60
- Cetearyl Alcohol
- Mineral Oil
- White Petrolatum
- Glycerin
- Lavandula Angustifolia (Lavender) Oil

Questions or comments?

Contact us at support@tagridstore.com